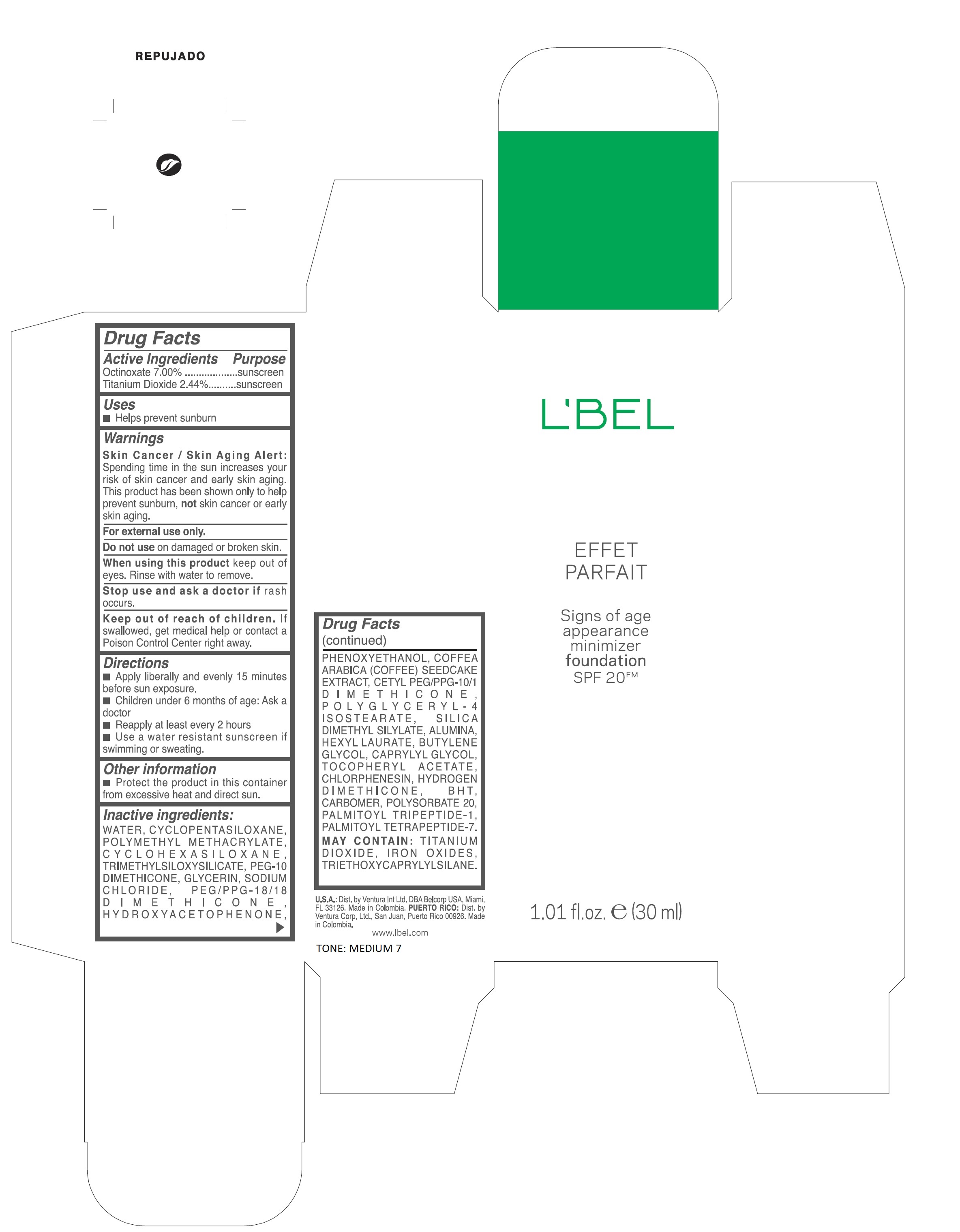 DRUG LABEL: LBEL EFFET PARFAIT SIGNS OF AGE APPEARANCE MINIMIZER FOUNDATION SPF 20 FM MEDIUM 7
NDC: 14783-292 | Form: EMULSION
Manufacturer: Ventura International LTD
Category: otc | Type: HUMAN OTC DRUG LABEL
Date: 20210729

ACTIVE INGREDIENTS: OCTINOXATE 7 g/100 mL; TITANIUM DIOXIDE 2.44 g/100 mL
INACTIVE INGREDIENTS: HYDROXYACETOPHENONE; PHENOXYETHANOL; CETYL PEG/PPG-10/1 DIMETHICONE (HLB 2); SODIUM CHLORIDE; POLYSORBATE 20; TRIETHOXYCAPRYLYLSILANE; .ALPHA.-TOCOPHEROL ACETATE; HEXYL LAURATE; PEG-10 DIMETHICONE (600 CST); PEG/PPG-18/18 DIMETHICONE; FERRIC OXIDE RED; GLYCERIN; CHLORPHENESIN; HYDROGEN DIMETHICONE (13 CST); BUTYLATED HYDROXYTOLUENE; CARBOMER HOMOPOLYMER, UNSPECIFIED TYPE; POLYGLYCERYL-4 ISOSTEARATE; SILICA DIMETHYL SILYLATE; ALUMINUM OXIDE; BUTYLENE GLYCOL; CYCLOMETHICONE 6; WATER; CYCLOMETHICONE 5; POLY(METHYL METHACRYLATE; 450000 MW); TRIMETHYLSILOXYSILICATE (M/Q 0.6-0.8)

L’BEL EFFET PARFAIT SIGNS OF AGE APPEARANCE MINIMIZER FOUNDATION SPF 20 FM

Active Ingredients Purpose

Octinoxate 7.00% Sunscreen

Titanium Dioxide 2.44% Sunscreen

Uses

Helps prevent sunburn

Keep out of reach of children. If swallowed, get medical help or contact a Poison Control Center right away.

Stop use and ask a doctor if rash occurs.

Warnings

Skin Cancer / Skin Aging Alert:

Spending time in the sun increases your risk of skin cancer and early skin aging. this product has shown only to help prevent sunburn, not skin cancer or early skin aging.

For external use only.

Do not use on damaged or broken skin.

when using this product keep out of eyes. Rinse with water to remove.

Directions

- Apply Liberally and evenly 15 minutes before sun exposure.
- Children under 6 months of age: ask a doctor
- Reapply at least every 2 hours
- use a water resistant sunscreen if swimming or sweating

Other Information

- Protect the product in this container from excessive heat and direct sun

Inactive ingredients:
WATER, CYCLOPENTASILOXANE, POLYMETHYL METHACRYLATE, CYCLOHEXASILOXANE, TRIMETHYLSILOXYSILICATE, PEG-10 DIMETHICONE, GLYCERIN, SODIUM CHLORIDE, PEG/PPG-18/18 DIMETHICONE, HYDROXYACETOPHENONE, PHENOXYETHANOL, COFFEA ARABICA (COFFEE) SEEDCAKE EXTRACT, CETYL PEG/PPG-10/1 DIMETHICONE, POLYGLYCERYL-4 ISOSTEARATE, SILICA DIMETHYL SILYLATE, ALUMINA, HEXYL LAURATE, BUTYLENE GLYCOL, CAPRYLYL GLYCOL, TOCOPHERYL ACETATE, CHLORPHENESIN, HYDROGEN DIMETHICONE, BHT, CARBOMER, POLYSORBATE 20, PALMITOYL TRIPEPTIDE-1, PALMITOYL TETRAPEPTIDE-7. MAY CONTAIN : TITANIUM DIOXIDE, IRON OXIDES, TRIETHOXYCAPRYLYLSILANE.

PACKAGE LABEL

L'BEL
EFFET PARFAIT
Signs of age appearance minimizer foundation SPF 20FM

1.01 fl. oz. (30 ml)

MEDIUM 7